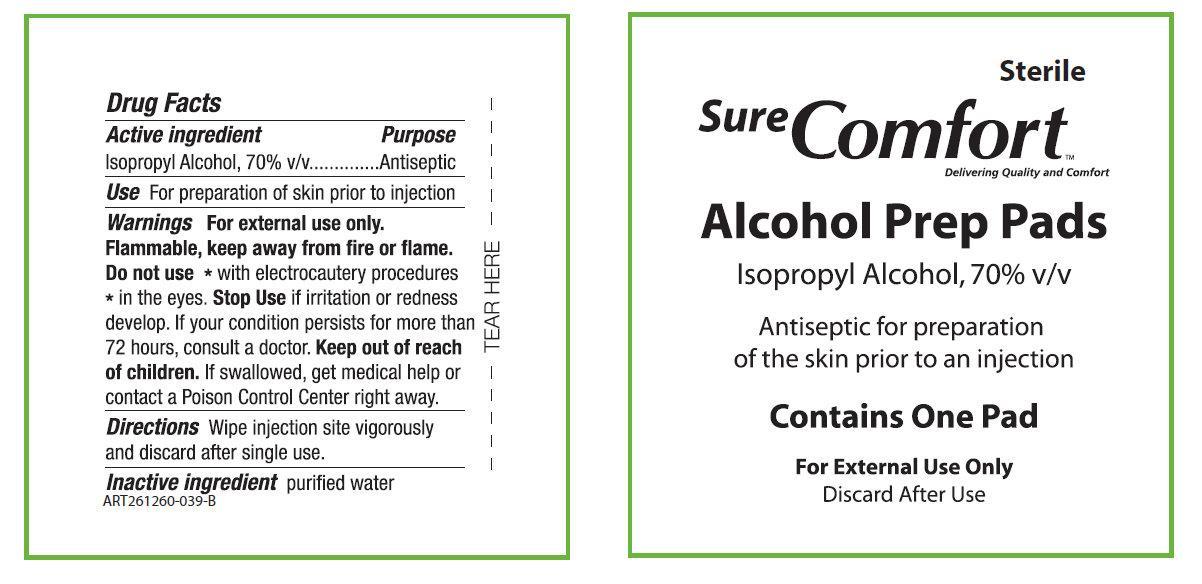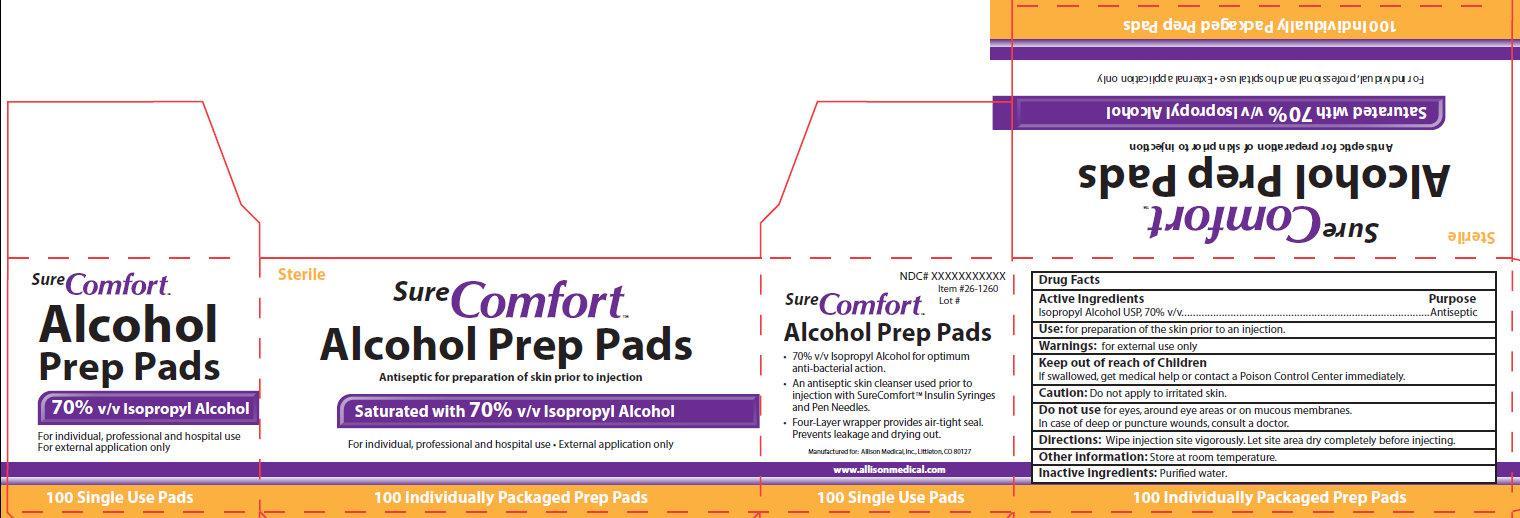 DRUG LABEL: SURE COMFORT ALCOHOL PREP PADS
NDC: 86227-000 | Form: SWAB
Manufacturer: Allison Medical Inc.
Category: otc | Type: HUMAN OTC DRUG LABEL
Date: 20171227

ACTIVE INGREDIENTS: ISOPROPYL ALCOHOL 70 mL/100 mL
INACTIVE INGREDIENTS: WATER

Sure Comfort Alcohol Prep Pads

Active Ingredients

Isopropyl Alcohol USP, 70% v/v

Purpose

Antiseptic

Use:

for preparation of the skin prior to injection.

Warnings

- For external use only.

Keep out of reach of Children

If swallowed, get medical help or contact a Poison Control Center immediately.

Caution:

Do not apply to irritated skin.

Do not use

for eyes, around eye areas or on mucous membranes.

In case of deep or puncture wounds, consult a doctor.

Directions

- Wipe injection site vigorously. Let site area dry completely before injecting.

Other information

Store at room temperature

Inactive Ingredients:

Purified water